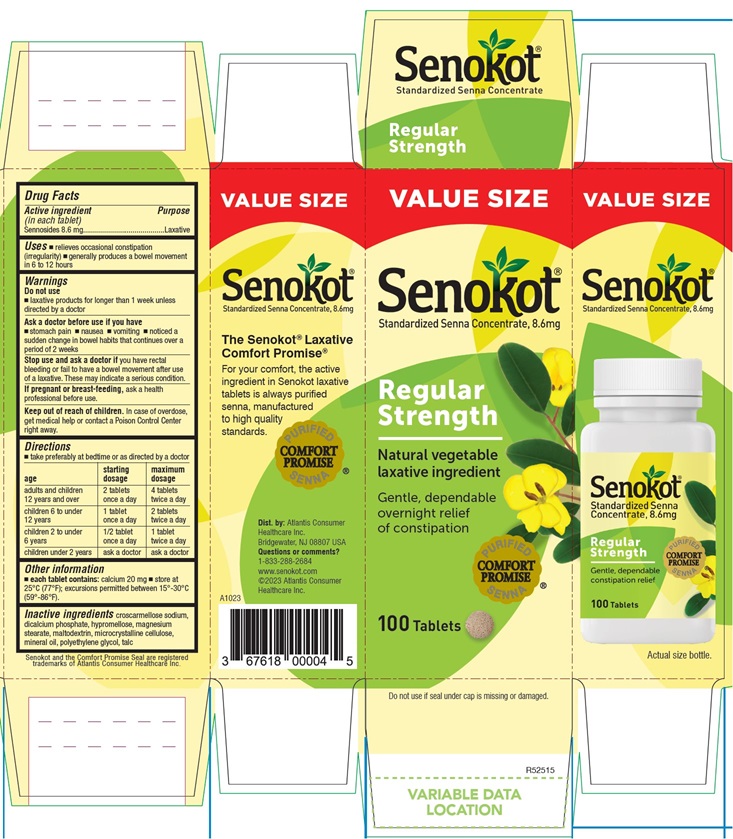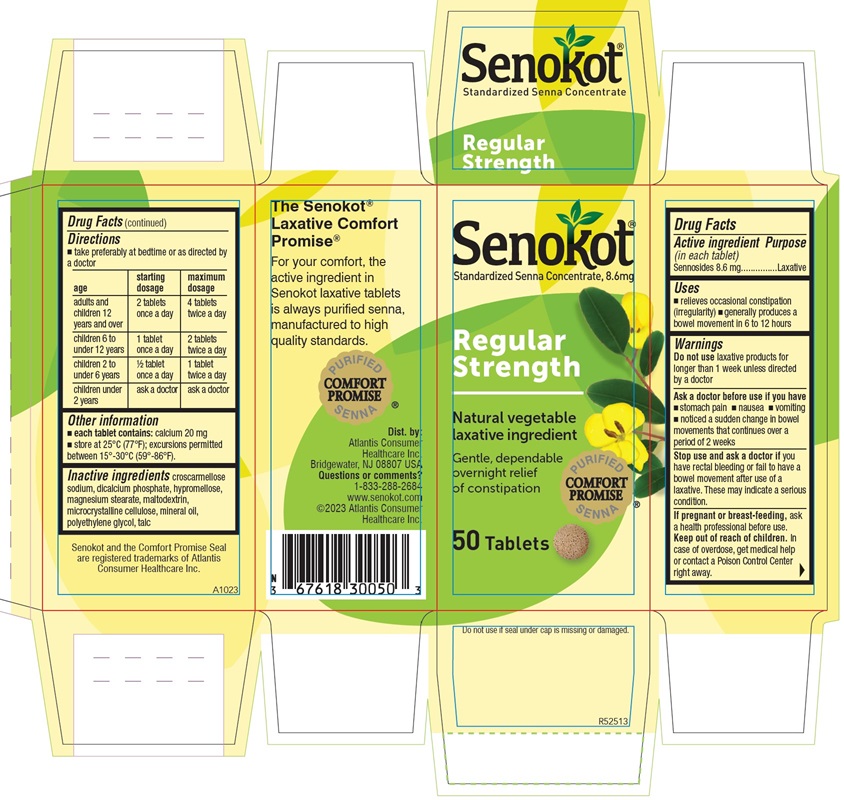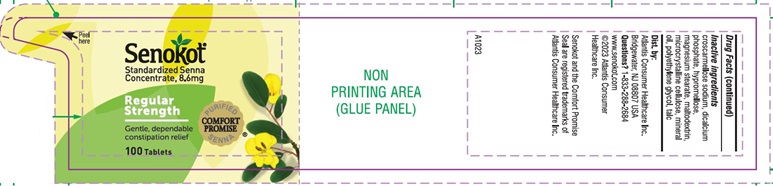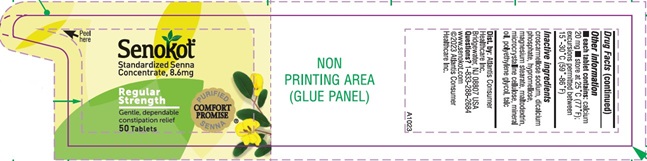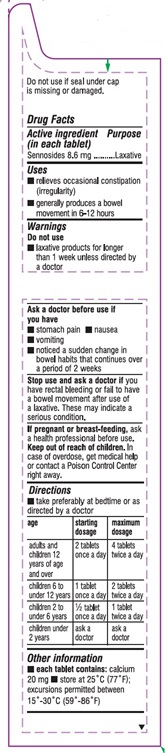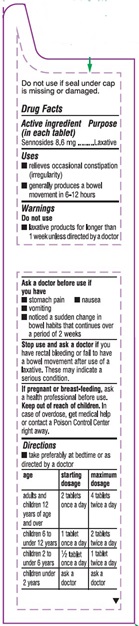 DRUG LABEL: Senokot
NDC: 67618-300 | Form: TABLET
Manufacturer: Atlantis Consumer Healthcare, Inc.
Category: otc | Type: HUMAN OTC DRUG LABEL
Date: 20251229

ACTIVE INGREDIENTS: SENNOSIDES 8.6 mg/1 1
INACTIVE INGREDIENTS: CROSCARMELLOSE SODIUM; CALCIUM PHOSPHATE, DIBASIC, ANHYDROUS; HYPROMELLOSE, UNSPECIFIED; MAGNESIUM STEARATE; MALTODEXTRIN; CELLULOSE, MICROCRYSTALLINE; MINERAL OIL; POLYETHYLENE GLYCOL, UNSPECIFIED; TALC

Senokot
(standardized senna concentrate)

Drug Facts
Active ingredient (in each tablet)

Sennosides 8.6mg

Purpose

Laxative

Uses

- relieves occasional constipation (irregularity)
- generally produces a bowel movement in 6–12 hours

Warnings

Do not use

- laxative products for longer than 1 week unless directed by a doctor

Aska doctor before use if you have

- stomach pain
- nausea
- vomiting
- noticed a sudden change in bowel habits that continues overa period of 2 weeks

Stop use and ask a doctorif you have rectal bleeding or fail to have a bowel movementafter use of a laxative. These may indicate a serious condition.

PREGNANCY OR BREAST FEEDING

If pregnant or breast-feeding, ask a health professional before use.

Keep out of reach of children. In case of overdose, get medical help or contact a Poison ControlCenter right away.

Directions

- take preferably at bedtime or as directed by a doctor

age | starting dosage | maximum dosage
adults and children 12 years of age and over | 2 tablets oncea day | 4 tablets twicea day
children 6 to under12 years | 1 tablet once aday | 2 tablets twicea day
children 2 to under6 years | 1/2 tablet oncea day | 1 tablet twicea day
children under2 years | ask a doctor | ask a doctor

Other Information

- each tablet contains: calcium 20 mg
- store at 25°C (77°F); excursions permitted between 15°-30°C (59°-86°F)

Inactive ingredients

croscarmellose sodium, dicalciumphosphate, hypromellose, magnesium stearate, maltodextrin, microcrystallinecellulose, mineral oil, polyethylene glycol, talc

©2020

Avrio Health L.P.

305616-0B

PACKAGE LABEL

50 Tablets
NDC 67618-300-50

100 Tablets
NDC 67618-300-10